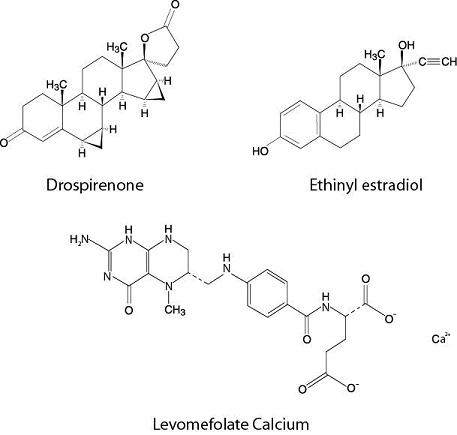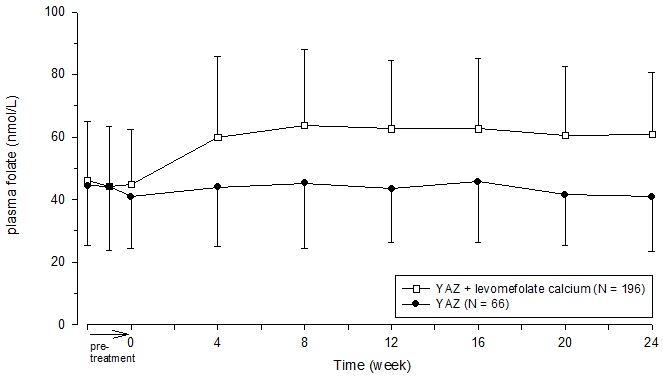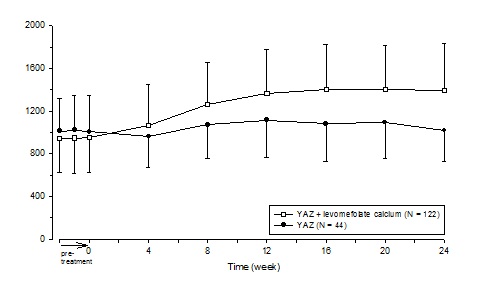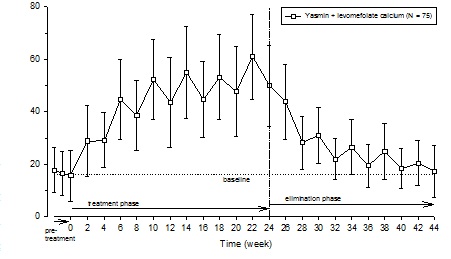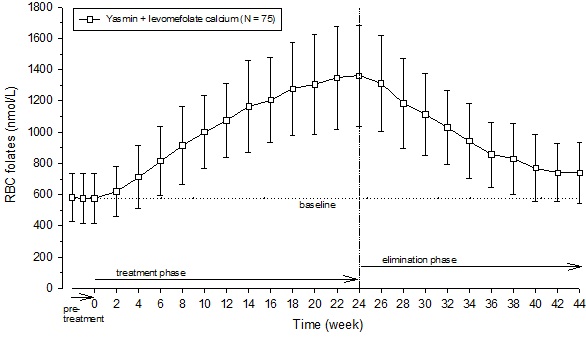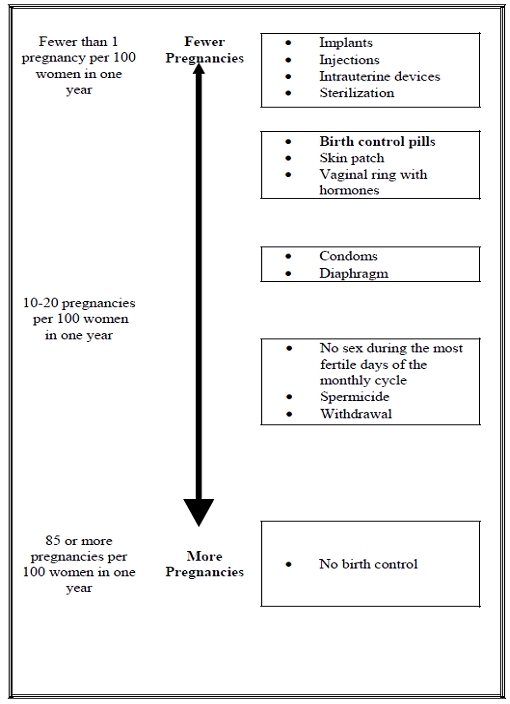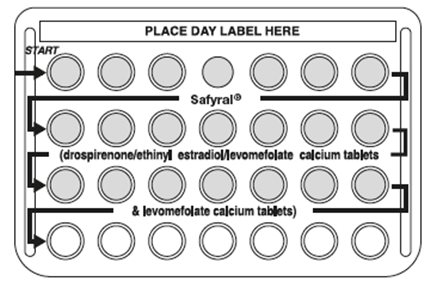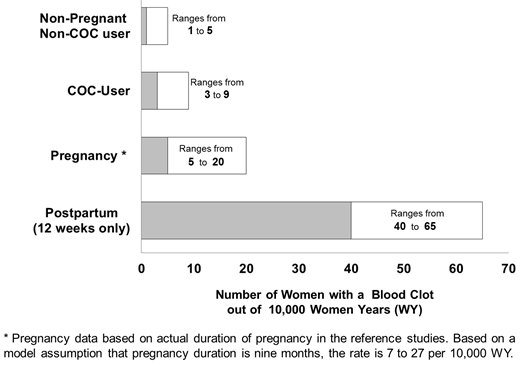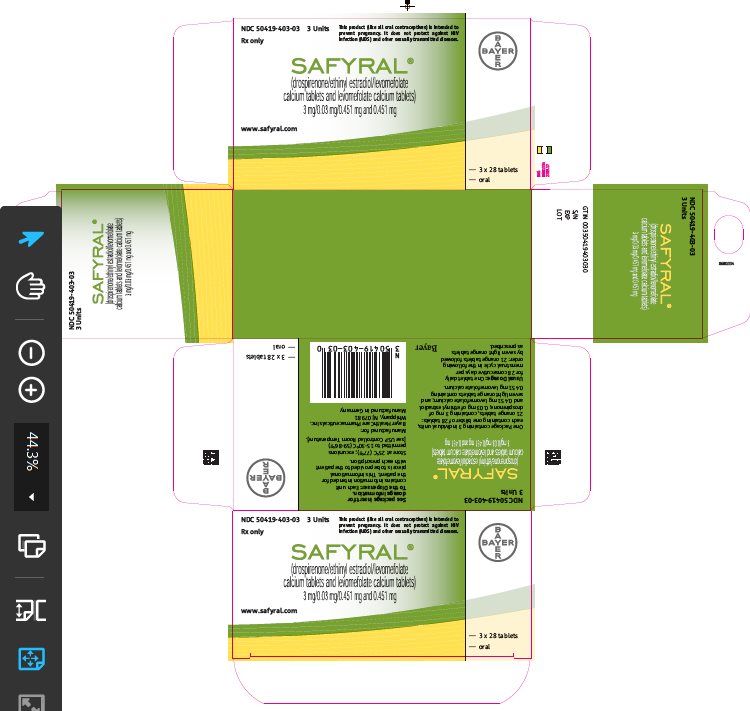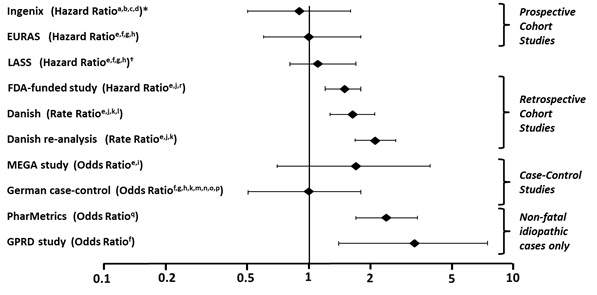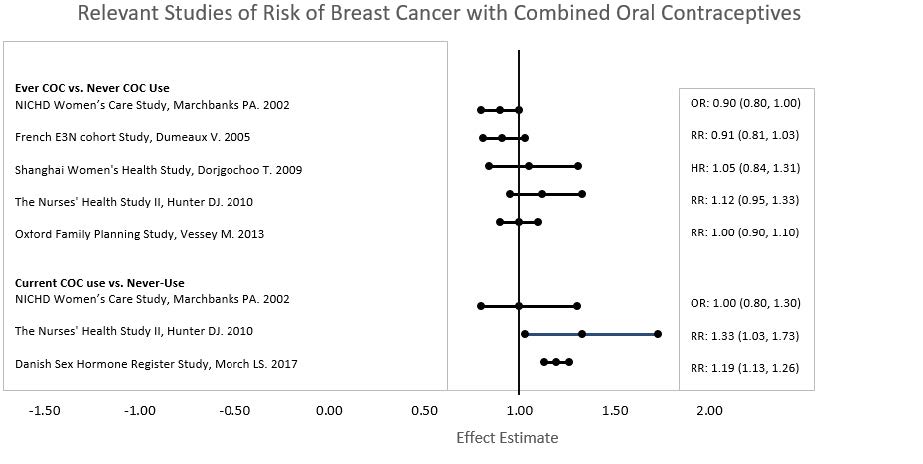 DRUG LABEL: Safyral
NDC: 50419-403 | Form: KIT | Route: ORAL
Manufacturer: Bayer HealthCare Pharmaceuticals Inc.
Category: prescription | Type: HUMAN PRESCRIPTION DRUG LABEL
Date: 20251219

ACTIVE INGREDIENTS: DROSPIRENONE 3 mg/1 1; ETHINYL ESTRADIOL 0.03 mg/1 1; LEVOMEFOLATE CALCIUM 0.451 mg/1 1; LEVOMEFOLATE CALCIUM 0.451 mg/1 1
INACTIVE INGREDIENTS: FERRIC OXIDE YELLOW; HYPROMELLOSE, UNSPECIFIED; LACTOSE MONOHYDRATE; MAGNESIUM STEARATE; TITANIUM DIOXIDE; BETADEX; MICROCRYSTALLINE CELLULOSE; CROSCARMELLOSE SODIUM; POLYETHYLENE GLYCOL, UNSPECIFIED; TALC; FERRIC OXIDE RED; HYPROMELLOSE, UNSPECIFIED; LACTOSE MONOHYDRATE; MAGNESIUM STEARATE; TALC; TITANIUM DIOXIDE; MICROCRYSTALLINE CELLULOSE; CROSCARMELLOSE SODIUM; HYDROXYPROPYL CELLULOSE (1600000 WAMW); POLYETHYLENE GLYCOL, UNSPECIFIED; FERRIC OXIDE RED; FERRIC OXIDE YELLOW

HIGHLIGHTS OF PRESCRIBING INFORMATION

These highlights do not include all the information needed to use SAFYRAL safely and effectively. See full prescribing information for SAFYRAL.
SAFYRAL (drospirenone/ethinyl estradiol/levomefolate calcium tablets and levomefolate calcium tablets) for oral use
Initial U.S. Approval: 2010

RECENT MAJOR CHANGES

Dosage and Administration (2.3) 5/2023

Contraindications, Pregnancy (4) Removed 5/2023

Warnings and Precautions (5.11) Removed 5/2023

WARNING: CIGARETTE SMOKING AND SERIOUS CARDIOVASCULAR EVENTS

See full prescribing information for complete boxed warning.

- Women over 35 years old who smoke should not use Safyral. (4)
- Cigarette smoking increases the risk of serious cardiovascular events from combination oral contraceptive (COC) use. (4)

1 INDICATIONS AND USAGE

Safyral is a combination of drospirenone, a progestin and ethinyl estradiol, an estrogen containing a folate, indicated for use by females of reproductive potential to:

- Prevent pregnancy. (1.1)
- Raise folate levels in females of reproductive potential who choose to use an oral contraceptive for contraception. (1.2)

2 DOSAGE AND ADMINISTRATION

- Take one tablet daily by mouth at the same time every day. (2.1)
- Tablets must be taken in the order directed on the blister pack. (2.1)

3 DOSAGE FORMS AND STRENGTHS

Safyral consists of 28 film-coated, biconvex tablets in the following order (3):

- 21 orange tablets, each containing 3 mg drospirenone (DRSP), 0.03 mg ethinyl estradiol (EE) as betadex clathrate and 0.451 mg levomefolate calcium
- 7 light orange tablets, each containing 0.451 mg levomefolate calcium

4 CONTRAINDICATIONS

- Renal impairment (4)
- Adrenal insufficiency (4)
- A high risk of arterial or venous thrombotic diseases (4)
- Undiagnosed abnormal uterine bleeding (4)
- Breast cancer (4)
- Liver tumors or liver disease (4)
- Co-administration with Hepatitis C drug combinations containing ombitasvir, paritaprevir/ritonavir, with or without dasabuvir (4)

5 WARNINGS AND PRECAUTIONS

- Vascular risks: Stop Safyral if a thrombotic event occurs. Stop at least 4 weeks before and through 2 weeks after major surgery. Start no earlier than 4 weeks after delivery, in women who are not breastfeeding. (5.1) COCs containing DRSP may be associated with a higher risk of venous thromboembolism (VTE) than COCs containing levonorgestrel or some other progestins. Before initiating Safyral in a new COC user or a woman who is switching from a contraceptive that does not contain DRSP, consider the risks and benefits of a DRSP-containing COC in light of her risk of a VTE. (5.1)
- Hyperkalemia: DRSP has anti-mineralocorticoid activity. Do not use in patients predisposed to hyperkalemia. Check serum potassium concentration during the first treatment cycle in women on long-term treatment with medications that may increase serum potassium concentration. (5.2, 7.1, 7.2)
- Liver disease: Discontinue Safyral if jaundice occurs. (5.4)
- High blood pressure: Do not prescribe Safyral for women with uncontrolled hypertension or hypertension with vascular disease. (5.6)
- Carbohydrate and lipid metabolic effects: Monitor prediabetic and diabetic women taking Safyral. Consider an alternate contraceptive method for women with uncontrolled dyslipidemia. (5.8)
- Headache: Evaluate significant change in headaches and discontinue Safyral if indicated. (5.9)
- Uterine bleeding: Evaluate irregular bleeding or amenorrhea. (5.10)

6 ADVERSE REACTIONS

- The most frequent adverse reactions (≥ 2%) in contraception and folate clinical trials are premenstrual syndrome (12.4%), headache /migraine (10.3%), breast pain/tenderness/discomfort (8.1%), nausea/vomiting (4.4%), mood changes (2.3%) and abdominal pain/tenderness/discomfort (2.2%). (6.1)

To report SUSPECTED ADVERSE REACTIONS, contact Bayer HealthCare Pharmaceuticals Inc. at 1-888-842-2937 or FDA at 1-800-FDA-1088 or www.fda.gov/medwatch

7 DRUG INTERACTIONS

- Drugs or herbal products that induce certain enzymes (for example, CYP3A4) may decrease the effectiveness of COCs or increase breakthrough bleeding. Counsel patients to use a back-up or alternative method of contraception when enzyme inducers are used with COCs. (7.1)

8 USE IN SPECIFIC POPULATIONS

Lactation: Can reduce milk production in breast-feeding females (8.2)

FULL PRESCRIBING INFORMATION

WARNING: CIGARETTE SMOKING AND SERIOUS CARDIOVASCULAR EVENTS

Cigarette smoking increases the risk of serious cardiovascular events from combination oral contraceptives (COC) use. This risk increases with age, particularly in women over 35 years of age, and with the number of cigarettes smoked. For this reason, COCs should not be used by women who are over 35 years of age and smoke [see Contraindications (4)].

1 INDICATIONS AND USAGE

1.1 Oral Contraceptive

Safyral is indicated for use by females of reproductive potential to prevent pregnancy.

1.2 Folate Supplementation

Safyral is indicated in females of reproductive potential who choose to use an oral contraceptive as their method of contraception, to raise folate levels for the purpose of reducing the risk of a neural tube defect in a pregnancy conceived while taking the product or shortly after discontinuing the product.

2 DOSAGE AND ADMINISTRATION

2.1 How to Take Safyral

Take one tablet by mouth at the same time every day. The failure rate may increase when pills are missed or taken incorrectly.

To achieve maximum contraceptive effectiveness, Safyral must be taken as directed, in the order directed on the blister pack. Single missed pills should be taken as soon as remembered.

2.2 How to Start Safyral

Instruct the patient to begin taking Safyral either on the first day of her menstrual period (Day 1 Start) or on the first Sunday after the onset of her menstrual period (Sunday Start).

Day 1 Start

During the first cycle of Safyral use, instruct the patient to take one orange Safyral daily, beginning on Day 1 of her menstrual cycle. (The first day of menstruation is Day 1.) She should take one orange Safyral daily for 21 consecutive days, followed by one light orange tablet, containing levomefolate alone, daily on Days 22 through 28. Safyral should be taken in the order directed on the package at the same time each day, preferably after the evening meal or at bedtime with some liquid, as needed. Safyral can be taken without regard to meals. If Safyral is first taken later than the first day of the menstrual cycle, Safyral should not be considered effective as a contraceptive until after the first 7 consecutive days of product administration. Instruct the patient to use a non-hormonal contraceptive as back-up during the first 7 days. The possibility of ovulation and conception prior to initiation of medication should be considered.

Sunday Start

During the first cycle of Safyral use, instruct the patient to take one orange Safyral daily, beginning on the first Sunday after the onset of her menstrual period. She should take one orange Safyral daily for 21 consecutive days, followed by one light orange tablet, containing levomefolate alone, daily on Days 22 through 28. Safyral should be taken in the order directed on the package at the same time each day, preferably after the evening meal or at bedtime with some liquid, as needed. Safyral can be taken without regard to meals. Safyral should not be considered effective as a contraceptive until after the first 7 consecutive days of product administration. Instruct the patient to use a non-hormonal contraceptive as back-up during the first 7 days. The possibility of ovulation and conception prior to initiation of medication should be considered.

The patient should begin her next and all subsequent 28-day regimens of Safyral on the same day of the week that she began her first regimen, following the same schedule. She should begin taking her orange tablets on the next day after ingestion of the last light orange folate tablet, regardless of whether or not a menstrual period has occurred or is still in progress. Anytime a subsequent cycle of Safyral is started later than the day following administration of the last light orange tablet, the patient should use another method of contraception until she has taken an orange Safyral daily for seven consecutive days.

When switching from a different birth control pill

When switching from another birth control pill, Safyral should be started on the same day that a new pack of the previous oral contraceptive would have been started.

When switching from a method other than a birth control pill

When switching from a transdermal patch or vaginal ring, Safyral should be started when the next application would have been due. When switching from an injection, Safyral should be started when the next dose would have been due. When switching from an intrauterine contraceptive or an implant, Safyral should be started on the day of removal.

Withdrawal bleeding usually occurs within 3 days following the last orange tablet. If spotting or breakthrough bleeding occurs while taking Safyral, instruct the patient to continue taking Safyral by the regimen described above. Counsel her that this type of bleeding is usually transient and without significance; however, advise her that if the bleeding is persistent or prolonged, she should consult her healthcare provider.

Although the occurrence of pregnancy is low if Safyral is taken according to directions, if withdrawal bleeding does not occur, consider the possibility of pregnancy. If the patient has not adhered to the prescribed dosing schedule (missed one or more active tablets or started taking them on a day later than she should have), consider the possibility of pregnancy at the time of the first missed period and take appropriate diagnostic measures. If the patient has adhered to the prescribed regimen and misses two consecutive periods, rule out pregnancy. Discontinue Safyral if pregnancy is confirmed.

The risk of pregnancy increases with each active orange tablet missed. If breakthrough bleeding occurs following missed tablets, it will usually be transient and of no consequence. If the patient misses one or more light orange tablets, she should still be protected against pregnancy provided she begins taking a new cycle of orange tablets on the proper day.

For postpartum women who do not breastfeed or after a second trimester abortion, start Safyral no earlier than 4 weeks postpartum due to the increased risk of thromboembolism. If the patient starts Safyral postpartum and has not yet had a period, evaluate for possible pregnancy, and instruct her to use an additional method of contraception until she has taken Safyral for 7 consecutive days.

2.3 Missed Doses

Table 1: Instructions for Safyral Missed Doses
If one orange active tablet is missed | Take it as soon as possible. Take the next tablet at the regular time. This means two tablets may be taken in one day. A back-up birth control method is not required if the patient has sex.
If two orange active tablets in a row are missed in Week 1 or Week 2 | Take two tablets as soon as possible and two tablets the next day. Then take one tablet a day until the pack is finished. Additional nonhormonal contraception (such as condoms and spermicide) should be used as back-up if the patient has sex within 7 days after missing tablets.
If two orange active tablets in a row are missed in Week 3 | Day 1 Start: Throw out the rest of the pack and start a new pack that same day.; Sunday Start: Keep taking one tablet every day until Sunday. On Sunday, throw out the rest of the pack and start a new pack that same day.; Additional nonhormonal contraception (such as condoms and spermicide) should be used as back-up if the patient has sex within 7 days after missing tablets. The patient may not have their period this month but this is expected. However, if they miss their period two months in a row, they should call their healthcare provider because they might be pregnant.
If three or more orange active tablets in a row are missed during any week | Day 1 Start: Throw out the rest of the pack and start a new pack that same day.; Sunday Start: Keep taking one tablet every day until Sunday. On Sunday, throw out the rest of the pack and start a new pack that same day.; Additional nonhormonal contraception (such as condoms and spermicide) should be used as back-up if the patient has sex within 7 days after missing tablets. The patient may not have their period this month but this is expected. However, if they miss their period two months in a row, they should call their healthcare provider because they might be pregnant.
If any of the seven light orange inactive tablets are missed in Week 4: | Throw away the tablets that were missed.; Keep taking one tablet each day until the pack is empty. They do not need a back-up method.
Finally, if they are still not sure what to do about the tablets they have missed: | Use nonhormonal contraception (such as condoms and spermicides) anytime they have sex. Contact their healthcare provider and continue taking one active orange tablet each day until otherwise directed.

2.4 Advice in Case of Gastrointestinal Disturbances

In case of severe vomiting or diarrhea, absorption may not be complete and additional contraceptive measures should be taken. If vomiting occurs within 3-4 hours after tablet-taking, this can be regarded as a missed tablet.

2.5 Folate Supplementation

The U.S. Preventive Services Task Force recommends that women of childbearing age consume supplemental folic acid in a dose of at least 0.4 mg (400 mcg) daily.^1 Consider other folate supplementation that a woman may be taking before prescribing Safyral. Ensure that folate supplementation is maintained if a woman discontinues Safyral due to pregnancy.

3 DOSAGE FORMS AND STRENGTHS

Safyral (drospirenone/ethinyl estradiol/levomefolate calcium tablets and levomefolate calcium tablets) is available in blister packs.

Each blister pack contains 28 film-coated, round, bi-convex tablets in the following order:

- 21 orange tablets each containing 3 mg drospirenone (DRSP), 0.03 mg ethinyl estradiol (EE) as betadex clathrate and 0.451 mg levomefolate calcium embossed with a “Y+” in a regular hexagon on one side
- 7 light orange tablets each containing 0.451 mg levomefolate calcium embossed with a “M+” in a regular hexagon on one side

4 CONTRAINDICATIONS

Safyral is contraindicated in females who are known to have or develop the following conditions:

- Renal impairment
- Adrenal insufficiency
- A high risk of arterial or venous thrombotic diseases. Examples include women who are known to:
- Smoke, if over age 35 [see Boxed Warning and Warnings and Precautions (5.1)]
- Have deep vein thrombosis or pulmonary embolism, now or in the past [see Warnings and Precautions (5.1)]
- Have cerebrovascular disease [see Warnings and Precautions (5.1)]
- Have coronary artery disease [see Warnings and Precautions (5.1)]
- Have thrombogenic valvular or thrombogenic rhythm diseases of the heart (for example, subacute bacterial endocarditis with valvular disease, or atrial fibrillation) [see Warnings and Precautions (5.1)]
- Have inherited or acquired hypercoagulopathies [see Warnings and Precautions (5.1)]
- Have uncontrolled hypertension [see Warnings and Precautions (5.6)]
- Have diabetes mellitus with vascular disease [see Warnings and Precautions (5.8)]
- Have headaches with focal neurological symptoms or have migraine headaches with or without aura if over age 35 [see Warnings and Precautions (5.9)]
- Undiagnosed abnormal uterine bleeding [see Warnings and Precautions (5.10)]
- Current diagnosis of, or history of, breast cancer, which may be hormone-sensitive [see Warnings and Precautions (5.3)]
- Liver tumor (benign or malignant) or liver disease [see Warnings and Precautions (5.4) and Use in Specific Populations (8.7)]
- Use of Hepatitis C drug combinations containing ombitasvir/paritaprevir/ritonavir, with or without dasabuvir due to the potential for ALT elevations [see Warnings and Precautions (5.5) and Drug Interactions (7.3)].

5 WARNINGS AND PRECAUTIONS

5.1 Thromboembolic Disorders and Other Vascular Problems

Stop Safyral if an arterial or venous thrombotic (VTE) event occurs.

Based on presently available information on DRSP-containing COCs with 0.03 mg ethinyl estradiol (that is, Yasmin), DRSP-containing COCs may be associated with a higher risk of venous thromboembolism (VTE) than COCs containing the progestin levonorgestrel or some other progestins. Epidemiologic studies that compared the risk of VTE reported that the risk ranged from no increase to a three-fold increase. Before initiating use of Safyral in a new COC user or a woman who is switching from a contraceptive that does not contain DRSP, consider the risks and benefits of a DRSP-containing COC in light of her risk of a VTE. Known risk factors for VTE include smoking, obesity, and family history of VTE, in addition to other factors that contraindicate use of COCs [see Contraindications (4)].

A number of studies have compared the risk of VTE for users of Yasmin (which contains 0.03 mg of EE and 3 mg of DRSP) to the risk for users of other COCs, including COCs containing levonorgestrel. Those that were required or sponsored by regulatory agencies are summarized in Table 2.

Table 2: Estimates (Hazard Ratios) of Venous Thromboembolism Risk in Current Users of Yasmin Compared to Users of Oral Contraceptives that Contain Other Progestins
Epidemiologic Study (Author, Year of Publication) Population Studied | Comparator Product (all are low-dose COCs; with ≤ 0.04 mg of EE) | Hazard Ratio (HR) (95% CI)
i3 Ingenix (Seeger 2007) Initiators, including new users ["New users" - no use of combination hormonal contraception for at least the prior 6 months] | All COCs available in the US during the conduct of the study [Includes low-dose COCs containing the following progestins: norgestimate, norethindrone, levonorgestrel, desogestrel, norgestrel, medroxyprogesterone, or ethynodiol diacetate] | HR: 0.9 (0.5-1.6)
EURAS (Dinger 2007) Initiators, including new users | All COCs available in Europe during the conduct of the study [Includes low-dose COCs containing the following progestins: levonorgestrel, desogestrel, dienogest, chlormadinone acetate, gestodene, cyproterone acetate, norgestimate, or norethindrone] | HR: 0.9 (0.6-1.4)
 | Levonorgestrel/EE | HR: 1.0 (0.6-1.8)
FDA-funded study” (2011)
New users | Other COCs available during the course of the study [Includes low-dose COCs containing the following progestins: norgestimate, norethindrone, or levonorgestrel] | HR: 1.8 (1.3-2.4)
 | Levonorgestrel/0.03 mg EE | HR: 1.6 (1.1-2.2)
All users (i.e., initiation and continuing use of study combination hormonal contraception) | Other COCs available during the course of the study | HR: 1.7 (1.4-2.1)
 | Levonorgestrel/0.03 mg EE | HR: 1.5 (1.2-1.8)

In addition to these “regulatory studies,” other studies of various designs have been conducted. Overall, there are two prospective cohort studies (see Table 2): the US post-approval safety study Ingenix [Seeger 2007], the European post-approval safety study EURAS (European Active Surveillance Study) [Dinger 2007]. An extension of the EURAS study, the Long-Term Active Surveillance Study (LASS), did not enroll additional subjects, but continued to assess VTE risk. There are three retrospective cohort studies: one study in the US funded by the FDA (see Table 2), and two from Denmark [Lidegaard 2009, Lidegaard 2011]. There are two case-control studies: the Dutch MEGA study analysis [van Hylckama Vlieg 2009] and the German case-control study [Dinger 2010]. There are two nested case-control studies that evaluated the risk of non-fatal idiopathic VTE: the PharMetrics study [Jick 2011] and the GPRD study [Parkin 2011]. The results of all of these studies are presented in Figure 1.

Figure 1: VTE Risk with Yasmin Relative to LNG-Containing COCs (adjusted risk#)

Risk ratios displayed on logarithmic scale; risk ratio < 1 indicates a lower risk of VTE for DRSP, > 1 indicates an increased risk of VTE for DRSP.

*Comparator “Other COCs” including LNG-containing COCs

† LASS is an extension of the EURAS study

#Some adjustment factors are indicated by superscript letters: a) Current heavy smoking, b) hypertension, c) obesity, d) family history, e) age, f) BMI, g) duration of use, h) VTE history, i) period of inclusion, j) calendar year, k) education, l) length of use, m) parity, n) chronic disease, o) concomitant medication, p) smoking, q) duration of exposure, r) site

(References: Ingenix [Seeger 2007]^2, EURAS (European Active Surveillance Study) [Dinger 2007]^3, LASS (Long-Term Active Surveillance Study) [Dinger, unpublished document on file], FDA-funded study [Sidney 2011]^4, Danish [Lidegaard 2009]^5, Danish re-analysis [ Lidegaard 2011]^6, MEGA study [van Hylckama Vlieg 2009]^7, German Case-Control study [Dinger 2010]^8, PharMetrics [Jick 2011]^9, GPRD study [Parkin 2011]^10)

Although the absolute VTE rates are increased for users of hormonal contraceptives compared to non-users, the rates during pregnancy are even greater, especially during the post-partum period (see Figure 2). The risk of VTE in women using COCs has been estimated to be 3 to 9 per 10,000 woman-years. The risk of VTE is highest during the first year of use. Data from a large, prospective cohort safety study of various COCs suggest that this increased risk, as compared to that in non-COC users, is greatest during the first 6 months of COC use. Data from this safety study indicate that the greatest risk of VTE is present after initially starting a COC or restarting (following a 4 week or greater pill-free interval) the same or a different COC.

The risk of thromboembolic disease due to oral contraceptives gradually disappears after COC use is discontinued.

Figure 2 shows the risk of developing a VTE for women who are not pregnant and do not use oral contraceptives, for women who use oral contraceptives, for pregnant women, and for women in the postpartum period. To put the risk of developing a VTE into perspective: If 10,000 women who are not pregnant and do not use oral contraceptives are followed for one year, between 1 and 5 of these women will develop a VTE.

Figure 2: Likelihood of Developing a VTE

If feasible, stop Safyral at least 4 weeks before and through 2 weeks after major surgery or other surgeries known to have an elevated risk of thromboembolism.

Start Safyral no earlier than 4 weeks after delivery, in women who are not breastfeeding. The risk of postpartum thromboembolism decreases after the third postpartum week, whereas the risk of ovulation increases after the third postpartum week.

Use of COCs also increases the risk of arterial thromboses such as strokes and myocardial infarctions, especially in women with other risk factors for these events.

COCs have been shown to increase both the relative and attributable risks of cerebrovascular events (thrombotic and hemorrhagic strokes), although, in general, the risk is greatest among older (>35 years of age), hypertensive women who also smoke. COCs also increase the risk for stroke in women with other underlying risk factors.

Oral contraceptives must be used with caution in women with cardiovascular disease risk factors.

Stop Safyral if there is unexplained loss of vision, proptosis, diplopia, papilledema, or retinal vascular lesions. Evaluate for retinal vein thrombosis immediately. [See Adverse Reactions (6).]

5.2 Hyperkalemia

Safyral contains 3 mg of the progestin DRSP, which has anti-mineralocorticoid activity, including the potential for hyperkalemia in high-risk patients, comparable to a 25 mg dose of spironolactone. Safyral is contraindicated in patients with conditions that predispose to hyperkalemia (that is, renal impairment, hepatic impairment, and adrenal insufficiency). Women receiving daily, long-term treatment for chronic conditions or diseases with medications that may increase serum potassium concentration should have their serum potassium concentration checked during the first treatment cycle. Medications that may increase serum potassium concentration include ACE inhibitors, angiotensin–II receptor antagonists, potassium-sparing diuretics, potassium supplementation, heparin, aldosterone antagonists, and NSAIDs. Consider monitoring serum potassium concentration in high-risk patients who take a strong CYP3A4 inhibitor long-term and concomitantly. Strong CYP3A4 inhibitors include azole antifungals (e.g. ketoconazole, itraconazole, voriconazole), HIV/HCV protease inhibitors (e.g., indinavir, boceprevir), and clarithromycin [see Clinical Pharmacology (12.3)].

5.3 Malignant Neoplasms

Breast Cancer

Safyral is contraindicated in females who currently have or have had breast cancer because breast cancer may be hormonally sensitive [see Contraindications (4)].

Epidemiology studies have not found a consistent association between use of combined oral contraceptives (COCs) and breast cancer risk. Studies do not show an association between ever (current or past) use of COCs and risk of breast cancer. However, some studies report a small increase in the risk of breast cancer among current or recent users (<6 months since last use) and current users with longer duration of COC use [see Adverse Reactions (6.2)].

Cervical Cancer

Some studies suggest that COCs are associated with an increase in the risk of cervical cancer or intraepithelial neoplasia. However, there is controversy about the extent to which these findings may be due to differences in sexual behavior and other factors.

5.4 Liver Disease

Discontinue Safyral if jaundice develops. Steroid hormones may be poorly metabolized in patients with impaired liver function. Acute or chronic disturbances of liver function may necessitate the discontinuation of COC use until markers of liver function return to normal and COC causation has been excluded.

Hepatic adenomas are associated with COC use. An estimate of the attributable risk is 3.3 cases/100,000 COC users. Rupture of hepatic adenomas may cause death through intra-abdominal hemorrhage.

Studies have shown an increased risk of developing hepatocellular carcinoma in long-term (> 8 years) COC users. However, the attributable risk of liver cancers in COC users is less than one case per million users.

Oral contraceptive-related cholestasis may occur in women with a history of pregnancy-related cholestasis. Women with a history of COC-related cholestasis may have the condition recur with subsequent COC use.

5.5 Risk of Liver Enzyme Elevations with Concomitant Hepatitis C Treatment

During clinical trials with the Hepatitis C combination drug regimen that contains ombitasvir/paritaprevir/ritonavir, with or without dasabuvir, ALT elevations greater than 5 times the upper limit of normal (ULN), including some cases greater than 20 times the ULN, were significantly more frequent in women using ethinyl estradiol-containing medications, such as COCs. Discontinue Safyral prior to starting therapy with the combination drug regimen ombitasvir/paritaprevir/ritonavir, with or without dasabuvir [see Contraindications (4)]. Safyral can be restarted approximately 2 weeks following completion of treatment with the Hepatitis C combination drug regimen.

5.6 High Blood Pressure

For women with well-controlled hypertension, monitor blood pressure and stop Safyral if blood pressure rises significantly. Women with uncontrolled hypertension or hypertension with vascular disease should not use COCs.

An increase in blood pressure has been reported in women taking COCs, and this increase is more likely in older women and with extended duration of use. The incidence of hypertension increases with increasing concentration of progestin.

5.7 Gallbladder Disease

Studies suggest a small increased relative risk of developing gallbladder disease among COC users.

5.8 Carbohydrate and Lipid Metabolic Effects

Carefully monitor prediabetic and diabetic women who are taking Safyral. COCs may decrease glucose tolerance in a dose-related fashion.

Consider alternative contraception for women with uncontrolled dyslipidemia. A small proportion of women will have adverse lipid changes while on COCs.

Women with hypertriglyceridemia, or a family history thereof, may be at an increased risk of pancreatitis when using COCs.

5.9 Headache

If a woman taking Safyral develops new headaches that are recurrent, persistent, or severe, evaluate the cause and discontinue Safyral if indicated.

An increase in frequency or severity of migraine during COC use (which may be prodromal of a cerebrovascular event) may be a reason for immediate discontinuation of the COC.

5.10 Bleeding Irregularities

Unscheduled (breakthrough or intracyclic) bleeding and spotting sometimes occur in patients on COCs, especially during the first three months of use. If bleeding persists or occurs after previously regular cycles, check for causes such as pregnancy or malignancy. If pathology and pregnancy are excluded, bleeding irregularities may resolve over time or with a change to a different COC.

Data from ten Yasmin contraceptive efficacy clinical trials (N=2,467) show that the percent of women who took Yasmin and experienced unscheduled bleeding decreased over time from 12% at cycle 2 to 6% (cycle 13). A total of 25 subjects out of 3,009 in the Yasmin and Safyral trials (<1%) discontinued due to bleeding complaints. These are described as metrorrhagia, vaginal hemorrhage, menorrhagia, abnormal withdrawal bleeding, and menometrorrhagia.

The average duration of scheduled bleeding episodes in the majority of subjects (86%–88%) was 4–7 days. Women who use Safyral may experience absence of withdrawal bleeding, even if they are not pregnant. Based on subject diaries from Yasmin contraceptive efficacy trials, during cycles 2–13, 1–11% of women per cycle experienced no withdrawal bleeding. Some women may encounter post-pill amenorrhea or oligomenorrhea, especially when such a condition was pre-existent.

If withdrawal bleeding does not occur, consider the possibility of pregnancy. If the patient has not adhered to the prescribed dosing schedule (missed one or more active tablets or started taking them on a day later than she should have), consider the possibility of pregnancy at the time of the first missed period and take appropriate diagnostic measures. If the patient has adhered to the prescribed regimen and misses two consecutive periods, rule out pregnancy.

5.11 Depression

Women with a history of depression should be carefully observed and Safyral discontinued if depression recurs to a serious degree.

5.12 Interference with Laboratory Tests

The use of COCs may change the results of some laboratory tests, such as coagulation factors, lipids, glucose tolerance, and binding proteins. Women on thyroid hormone replacement therapy may need increased doses of thyroid hormone because serum concentrations of thyroid-binding globulin increase with use of COCs [see Drug Interactions (7.2)].

DRSP causes an increase in plasma renin activity and plasma aldosterone induced by its mild anti-mineralocorticoid activity.

Folates may mask vitamin B12 deficiency.

5.13 Monitoring

A woman who is taking COCs should have a yearly visit with her healthcare provider for a blood pressure check and for other indicated healthcare.

5.14 Other Conditions

In women with hereditary angioedema, exogenous estrogens may induce or exacerbate symptoms of angioedema. Chloasma may occasionally occur, especially in women with a history of chloasma gravidarum. Women with a tendency to chloasma should avoid exposure to the sun or ultraviolet radiation while taking COCs.

6 ADVERSE REACTIONS

The following serious adverse reactions with the use of COCs are discussed elsewhere in the labeling:

- Serious cardiovascular events and stroke [see Boxed Warning and Warnings and Precautions (5.1)]
- Vascular events [see Warnings and Precautions (5.1)]
- Liver disease [see Warnings and Precautions (5.4)]

6.1 Clinical Trials Experience

Because clinical trials are conducted under widely varying conditions, the adverse reaction rates observed cannot be directly compared to rates in other clinical trials and may not reflect the rates observed in practice.

Contraception and Folate Supplementation Clinical Trials

The data provided reflect the experience with the use of Yasmin (3 mg DRSP/0.03 mg EE) in the adequate and well-controlled studies for contraception (N=2,837) and folate supplementation (N=172). For contraception, the US pivotal clinical study (N=326) for the oral contraception indication for Yasmin was a multicenter, open-label trial in healthy women aged 18–35 who were treated with Yasmin for up to 13 cycles. The second contraceptive pivotal study (N=442) was a multicenter, randomized, open-label comparative European study of Yasmin vs. 0.150 mg desogestrel/0.03 mg EE conducted in healthy women aged 17–40 who were treated for up to 26 cycles. The primary efficacy study using Safyral for folate supplementation was a randomized, single-center European trial in 172 healthy, female subjects aged 18–40 years comparing the pharmacodynamic effects of Yasmin + 0.451 mg levomefolate calcium to Yasmin co-administered with folic acid during 24 weeks of treatment followed by 20 weeks of open-label Yasmin.

The adverse reactions seen across the 2 indications overlapped and are reported using the frequencies from the pooled dataset. The most common adverse reactions (≥ 2% of users) were: premenstrual syndrome (12.4%), headache/migraine (10.3%), breast pain/tenderness/discomfort (8.1%), nausea/vomiting (4.4%), mood changes (depression, depressed mood, irritability, mood swings, mood altered and affect lability (2.3%), and abdominal pain/discomfort/tenderness (2.2%).

Adverse Reactions (≥1%) Leading to Study Discontinuation

Contraception Clinical Trials

Of 2,837 women, 6.7% discontinued from the clinical trials due to an adverse reaction; the most frequent adverse reaction leading to discontinuation was headache/migraine (1.5%).

Folate Clinical Trial

There were no subjects who discontinued due to an adverse reaction.

Serious Adverse Reactions:

Contraception Clinical Trials: depression, pulmonary embolism, toxic skin eruption, and uterine leiomyoma.

Folate Supplementation Clinical Trial: none reported in the clinical trial

6.2 Postmarketing Experience

Five studies that compared breast cancer risk between ever-users (current or past use) of COCs and never-users of COCs reported no association between ever use of COCs and breast cancer risk, with effect estimates ranging from 0.90 - 1.12 (Figure 3).

Three studies compared breast cancer risk between current or recent COC users (<6 months since last use) and never users of COCs (Figure 3). One of these studies reported no association between breast cancer risk and COC use. The other two studies found an increased relative risk of 1.19 - 1.33 with current or recent use. Both of these studies found an increased risk of breast cancer with current use of longer duration, with relative risks ranging from 1.03 with less than one year of COC use to approximately 1.4 with more than 8-10 years of COC use.

Figure 3: Relative Studies of Risk of Breast Cancer with Combined Oral Contraceptives

RR = relative risk; OR = odds ratio; HR = hazard ratio. “ever COC” are females with current or past COC use; “never COC use” are females that never used COCs.

The following adverse reactions have been identified during post-approval use of Yasmin. Because these reactions are reported voluntarily from a population of uncertain size, it is not always possible to reliably estimate their frequency or establish a causal relationship to drug exposure.

Adverse reactions, including fatalities, are grouped into System Organ Classes and ordered by frequency.

Vascular disorders: Venous and arterial thromboembolic events (including pulmonary emboli, deep vein thrombosis, intracardiac thrombosis, intracranial venous sinus thrombosis, sagittal sinus thrombosis, retinal vein occlusion, myocardial infarction and stroke), hypertension

Hepatobiliary disorders: Gallbladder disease

Immune system disorders: Hypersensitivity

Metabolism and nutrition disorders: Hyperkalemia

Skin and subcutaneous tissue disorders: Chloasma

7 DRUG INTERACTIONS

Consult the labeling of all concurrently-used drugs to obtain further information about interactions with hormonal contraceptives or the potential for enzyme alterations.

7.1 Effects of Other Drugs on Combined Oral Contraceptives

Substances diminishing the efficacy of COCs: Drugs or herbal products that induce certain enzymes, including cytochrome P450 3A4 (CYP3A4), may decrease the effectiveness of COCs or increase breakthrough bleeding. Some drugs or herbal products that may decrease the effectiveness of hormonal contraceptives include phenytoin, barbiturates, carbamazepine, bosentan, felbamate, griseofulvin, oxcarbazepine, rifampin, topiramate and products containing St. John’s wort. Interactions between oral contraceptives and other drugs may lead to breakthrough bleeding and/or contraceptive failure. Counsel women to use an alternative method of contraception or a back-up method when enzyme inducers are used with COCs, and to continue back-up contraception for 28 days after discontinuing the enzyme inducer to ensure contraceptive reliability.

Substances increasing the plasma concentrations of COCs: Co-administration of atorvastatin with certain COCs containing EE increase AUC values for EE by approximately 20%. Ascorbic acid and acetaminophen may increase plasma EE concentrations, possibly by inhibition of conjugation.

Concomitant administration of moderate or strong CYP3A4 inhibitors such as azole antifungals (e.g., ketoconazole, itraconazole, voriconazole, fluconazole), verapamil, macrolides (e.g., clarithromycin, erythromycin), diltiazem, and grapefruit juice can increase the plasma concentrations of the estrogen or the progestin or both. In a clinical drug-drug interaction study conducted in premenopausal women, once daily co-administration of DRSP 3 mg/EE 0.02 mg containing tablets with strong CYP3A4 inhibitor, ketoconazole 200 mg twice daily for 10 days resulted in a moderate increase of DRSP systemic exposure. The exposure of EE was increased mildly [see Warnings and Precautions (5.2) and Clinical Pharmacology (12.3)].

Human immunodeficiency virus (HIV)/Hepatitis C virus (HCV) protease inhibitors and non-nucleoside reverse transcriptase inhibitors: Significant changes (increase or decrease) in the plasma concentrations of estrogen and progestin have been noted in some cases of co-administration with HIV/HCV protease inhibitors or with non-nucleoside reverse transcriptase inhibitors.

Antibiotics: There have been reports of pregnancy while taking hormonal contraceptives and antibiotics, but clinical pharmacokinetic studies have not shown consistent effects of antibiotics on plasma concentrations of synthetic steroids.

7.2 Effects of Combined Oral Contraceptives on Other Drugs

COCs containing EE may inhibit the metabolism of other compounds. COCs have been shown to significantly decrease plasma concentrations of lamotrigine, likely due to induction of lamotrigine glucuronidation. This may reduce seizure control; therefore, dosage adjustments of lamotrigine may be necessary. Consult the labeling of the concurrently-used drug to obtain further information about interactions with COCs or the potential for enzyme alterations.

COCs Increasing the Plasma Concentrations of CYP450 Enzymes: In clinical studies, administration of a hormonal contraceptive containing EE did not lead to any increase or only to a weak increase in plasma concentrations of CYP3A4 substrates (e.g., midazolam) while plasma concentrations of CYP2C19 substrates (e.g., omeprazole and voriconazole) and CYP1A2 substrates (e.g., theophylline and tizanidine) can have a weak or moderate increase.

Clinical studies did not indicate an inhibitory potential of DRSP towards human CYP enzymes at clinically relevant concentrations [see Clinical Pharmacology (12.3)].

Women on thyroid hormone replacement therapy may need increased doses of thyroid hormone because serum concentration of thyroid-binding globulin increases with use of COCs.

Potential to Increase Serum Potassium Concentration: There is a potential for an increase in serum potassium concentration in women taking Safyral with other drugs that may increase serum potassium concentration [see Warnings and Precautions (5.2) and Clinical Pharmacology (12.3)].

7.3 Concomitant Use with HCV Combination Therapy – Liver Enzyme Elevation

Do not co-administer Safyral with HCV drug combinations containing ombitasvir/paritaprevir/ritonavir, with or without dasabuvir, due to potential for ALT elevations [see Warnings and Precautions (5.5)].

7.4 Effects of Folates on Other Drugs

Folates may modify the pharmacokinetics or pharmacodynamics of certain antifolate drugs, e.g., antiepileptics (such as phenytoin), methotrexate or pyrimethamine, and may result in a decreased pharmacological effect of the antifolate drug.

7.5 Effects of Other Drugs on Folates

Several drugs have been reported to reduce folate concentrations by inhibition of the dihydrofolate reductase enzyme
(e.g., methotrexate and sulfasalazine) or by reducing folate absorption (e.g., cholestyramine), or via unknown mechanisms (e.g., antiepileptics such as carbamazepine, phenytoin, phenobarbital, primidone and valproic acid).

7.6 Interference with Laboratory Tests

The use of contraceptive steroids may influence the results of certain laboratory tests, such as coagulation factors, lipids, glucose tolerance, and binding proteins. DRSP causes an increase in plasma renin activity and plasma aldosterone induced by its mild anti-mineralocorticoid activity. Folates may mask vitamin B12 deficiency. [See Warnings and Precautions (5.12) and Drug Interactions (7.2).]

8 USE IN SPECIFIC POPULATIONS

8.1 Pregnancy

Risk Summary

There is no use for contraception in pregnancy; therefore, Safyral should be discontinued during pregnancy. Epidemiologic studies and meta-analyses have not found an increased risk of genital or non-genital birth defects (including cardiac anomalies and limb-reduction defects) following exposure to CHCs before conception or during early pregnancy. In the U.S. general population, the estimated background risk of major birth defects and miscarriage in clinically recognized pregnancies is 2 to 4 percent and 15 to 20 percent, respectively.

Data

Human Data

A retrospective database study of women in Norway, that included 44,734 pregnancies of which 368 were women who inadvertently took drospirenone/ethinyl estradiol during the first trimester of a pregnancy, found there were no adverse effects on pre-term birth, small for gestational age, or birth weight Z-scores.

Post-marketing adverse event data on the use of Safyral in pregnant women suggest that frequencies of miscarriage and congenital anomalies were not higher than the estimated background risk in the general population.

8.2 Lactation

Risk Summary

DRSP is present in human milk. After a single oral administration of 3 mg DRSP/0.03 mg EE tablets, DRSP concentration in breast milk over the 24-h period ranged from 1.4 to 7.0 ng/mL, with a mean ± standard deviation value of 3.7 ± 1.9 ng/mL.The estimated mean infant dose was 0.003 mg/day, which is about 0.1% of maternal dose (see Data).There is limited information on the effects of Safyral on the breast-fed infant. CHCs can reduce milk production in breast-feeding females. This reduction can occur at any time but is less likely to occur once breast-feeding is well-established. When possible, advise the nursing female to use other methods of contraception until she discontinues breast-feeding [See also Dosage and Administration (2.2)]. Increase in folate concentration in milk is not expected (see Data).

The developmental and health benefits of breast-feeding should be considered along with the mother’s clinical need for Safyral and any potential adverse effects on the breast-fed child from Safyral or from the underlying maternal condition.

Data

Human Data

An open-label study evaluated the degree of DRSP transfer into milk within 72 hours following a single oral administration of 3 mg DRSP/0.03 mg EE tablets to 6 healthy lactating women who were 1 week to 3 months post-partum. DRSP was present in breast milk with a mean Cmax of 13.5 ng/mL, while the mean Cmax in serum of lactating women was 30.8 ng/mL. The DRSP concentration in breast milk over the 24-hour period following dosing ranged from 1.4 to 7.0 ng/mL, with a mean ± standard deviation value of 3.7 ± 1.9 ng/mL. Based on single dose data, the maximal daily infant dose of DRSP was calculated to be 0.003 mg/day, which represented a mean of 0.1% of the maternal dose.

A study in approximately 60 lactating women demonstrated no significant differences in folate concentrations in milk between women who received 416 mcg/day [6S]-5-methyltetrahydrofolate or 400 mcg/day folic acid and women who received placebo over a 16-week period. Studies to date indicate there is no adverse effect of folate on nursing infants.

8.4 Pediatric Use

Safety and efficacy of Safyral has been established in women of reproductive age. Efficacy is expected to be the same for postpubertal adolescents under the age of 18 and for users 18 years and older. Use of this product before menarche is not indicated.

8.5 Geriatric Use

Safyral has not been studied in postmenopausal women and is not indicated in this population.

8.6 Patients with Renal Impairment

Safyral is contraindicated in patients with renal impairment [see Contraindications (4) and Warnings and Precautions (5.2)].

In subjects with creatinine clearance (CLcr) of 50–79 mL/min, serum DRSP concentrations were comparable to those in a control group with CLcr ≥ 80 mL/min. In subjects with CLcr of 30–49 mL/min, serum DRSP concentrations were on average 37% higher than those in the control group. In addition, there is a potential to develop hyperkalemia in subjects with renal impairment whose serum potassium is in the upper reference range, and who are concomitantly using potassium-sparing drugs [see Clinical Pharmacology (12.3)].

8.7 Patients with Hepatic Impairment

Safyral is contraindicated in patients with hepatic disease [see Contraindications (4) and Warnings and Precautions (5.4)]. The mean exposure to DRSP in women with moderate liver impairment is approximately three times higher than the exposure in women with normal liver function. Safyral has not been studied in women with severe hepatic impairment.

8.8 Race

No clinically significant difference was observed between the pharmacokinetics of DRSP or EE in Japanese versus Caucasian women [see Clinical Pharmacology (12.3)].

10 OVERDOSAGE

There have been no reports of serious ill effects from overdose, including ingestion by children. Overdosage may cause withdrawal bleeding in females and nausea.

DRSP is a spironolactone analogue which has anti-mineralocorticoid properties. Serum concentration of potassium and sodium, and evidence of metabolic acidosis, should be monitored in cases of overdose.

Levomefolate calcium doses of 17 mg/day (37-fold higher than the levomefolate calcium dose of Safyral) were well tolerated after long-term treatment up to 12 weeks.

11 DESCRIPTION

Safyral (drospirenone/ethinyl estradiol/levomefolate calcium tablets and levomefolate calcium tablets) provides an oral contraceptive regimen consisting of 28 film-coated tablets that contain the active ingredients specified for each tablet below:

- 21 orange tablets each containing 3 mg DRSP, 0.03 mg EE as betadex clathrate, and 0.451 mg levomefolate calcium
- 7 light orange tablets each containing 0.451 mg levomefolate calcium

The inactive ingredients in the orange tablets are lactose monohydrate NF, microcrystalline cellulose NF, croscarmellose sodium NF, hydroxypropyl cellulose USP, magnesium stearate NF, hypromellose USP, titanium dioxide USP, talc USP, polyethylene glycol NF, ferric oxide pigment, yellow NF, and ferric oxide pigment, red NF. The light orange film-coated tablets contain 0.451 mg of levomefolate calcium. The inactive ingredients in the light orange tablets are lactose monohydrate NF, microcrystalline cellulose NF, croscarmellose sodium NF, hydroxypropyl cellulose NF, magnesium stearate NF, hypromellose USP, titanium dioxide USP, talc USP, polyethylene glycol NF and ferric oxide pigment, yellow NF, and ferric oxide pigment, red NF.

Drospirenone (6R,7R,8R,9S,10R,13S,14S,15S,16S,17S)-1,3',4',6,6a,7,8,9,10,11,12,13, 14,15,15a,16-hexadecahydro-10,13-dimethylspiro-[17H-dicyclopropa-[6,7:15,16] cyclopenta[a]phenanthrene-17,2'(5H)-furan]-3,5'(2H)-dione) is a synthetic progestational compound and has a molecular weight of 366.5 and a molecular formula of C24H30O3.

Ethinyl estradiol (19-nor-17α-pregna 1,3,5(10)-triene-20-yne-3,17-diol) is a synthetic estrogenic compound and has a molecular weight of 296.4 and a molecular formula of C20H24O2.

Levomefolate calcium (N-[4-[[(2-amino-1,4,5,6,7,8-hexahydro-5-methyl-4-oxo-(6S)-pteridinyl)methyl]amino]benzoyl]-L-glutamic acid, calcium salt) is a synthetic calcium salt of L-5-methyltetrahydrofolate (L-5-methyl-THF), which is a metabolite of vitamin B9 and has a molecular weight of 497.5 and a molecular formula of C20H23CaN7O6.

The structural formulas are as follows:

12 CLINICAL PHARMACOLOGY

12.1 Mechanism of Action

COCs lower the risk of becoming pregnant primarily by suppressing ovulation.

12.2 Pharmacodynamics

Drospirenone is a spironolactone analogue with anti-mineralocorticoid activity. The estrogen in Safyral is ethinyl estradiol (EE).

Contraception

No specific pharmacodynamic studies were conducted with Safyral.

Folate Supplementation

Two studies evaluated the impact of Safyral on plasma folate and red blood cell (RBC) folate levels. A randomized, double-blind, active-controlled, parallel group study compared plasma folate and RBC folate levels during a 24-week treatment with 3 mg DRSP/0.02 mg EE (YAZ)+0.451 mg levomefolate calcium as compared to YAZ alone in a U.S. population. The pharmacodynamic effect on plasma folate, RBC folate, and the profile of circulating folate metabolites was assessed during 24 weeks of treatment with 0.451 mg levomefolate calcium or with 0.4 mg folic acid (equimolar dose to 0.451 mg levomefolate calcium), both in combination with 3 mg DRSP/0.03 mg EE (Yasmin) followed by 20 weeks of open-label treatment with Yasmin only (elimination phase). [See Clinical Studies, (14.2).]

12.3 Pharmacokinetics

Absorption

Safyral and Yasmin are bioequivalent with respect to DRSP and EE.

The absolute bioavailability of DRSP from a single entity tablet is about 76%. The absolute bioavailability of EE is approximately 40% as a result of presystemic conjugation and first-pass metabolism. The absolute bioavailability of Safyral, which is a combination tablet of DRSP and EE stabilized by betadex as a clathrate (molecular inclusion complex), has not been evaluated. The bioavailability of EE is similar when dosed via a betadex clathrate formulation compared to when it is dosed as a free steroid. Serum concentrations of DRSP and EE reached peak levels within 1–2 hours after administration of Safyral.

The pharmacokinetics of DRSP are dose proportional following single doses ranging from 1-10 mg. Following daily dosing of Yasmin, steady state DRSP concentrations were observed after 8 days. There was about 2 to 3 fold accumulation in serum Cmax and AUC (0–24h) values of DRSP following multiple dose administration of Yasmin (see Table 3).

For EE, steady-state conditions are reported during the second half of a treatment cycle. Following daily administration of Yasmin serum Cmax and AUC (0-24h) values of EE accumulate by a factor of about 1.5 to 2 (see Table 3).

Levomefolate calcium is structurally identical to L-5-methyltetrahydrofolate (L-5-methyl-THF), a metabolite of vitamin B9. Mean baseline concentrations of about 15 nmol/L are reached in populations without folate food fortification under normal nutritional conditions. Orally administered levomefolate calcium is absorbed and is incorporated into the body folate pool. Peak plasma concentrations of about 50 nmol/L above baseline are reached within 0.5–1.5 hours after single oral administration of 0.451 mg levomefolate calcium.

Steady state conditions for total folate in plasma after intake of 0.451 mg levomefolate calcium are reached after about 8–16 weeks depending on the baseline levels. In red blood cells achievement of steady state is delayed due to the long life-span of red blood cells of about 120 days.

Table 3: Mean Pharmacokinetic Parameters of Yasmin (DRSP 3 mg and EE 0.03 mg)
DRSP
Mean (%CV) Values
Cycle / Day | No. of Subjects | Cmax (ng/mL) | Tmax (h) | AUC(0-24h) (ng•h/mL) | t1/2 (h)
1/1 | 12 | 36.9 (13) | 1.7 (47) | 288 (25) | NA [NA - Not available]
1/21 | 12 | 87.5 (59) | 1.7 (20) | 827 (23) | 30.9 (44)
6/21 | 12 | 84.2 (19) | 1.8 (19) | 930 (19) | 32.5 (38)
9/21 | 12 | 81.3 (19) | 1.6 (38) | 957 (23) | 31.4 (39)
13/21 | 12 | 78.7 (18) | 1.6 (26) | 968 (24) | 31.1 (36)
EE
Mean (%CV) Values
Cycle/Day | No. of Subjects | Cmax (pg/mL) | Tmax (h) | AUC(0-24h) (pg•h/mL) | t1/2 (h)
1/1 | 11 | 53.5 (43) | 1.9 (45) | 280 (87) | NA
1/21 | 11 | 92.1 (35) | 1.5 (40) | 461 (94) | NA
6/21 | 11 | 99.1 (45) | 1.5 (47) | 346 (74) | NA
9/21 | 11 | 87 (43) | 1.5 (42) | 485 (92) | NA
13/21 | 10 | 90.5 (45) | 1.6 (38) | 469 (83) | NA

Food Effect

The rate of absorption of DRSP and EE following single administration of a formulation similar to Safyral was slower under fed (high fat meal) conditions with the serum Cmax being reduced about 40% for both components. The extent of absorption of DRSP, however, remained unchanged. In contrast, the extent of absorption of EE was reduced by about 20% under fed conditions.

The effect of food on absorption of levomefolate calcium following administration of Safyral has not been evaluated.

Distribution

DRSP and EE serum concentrations decline in two phases. The apparent volume of distribution of DRSP is approximately 4 L/kg and that of EE is reported to be approximately 4–5 L/kg.

DRSP does not bind to sex hormone binding globulin (SHBG) or corticosteroid binding globulin (CBG) but binds about 97% to other serum proteins. Multiple dosing over 3 cycles resulted in no change in the free fraction (as measured at trough concentrations). EE is reported to be highly but non-specifically bound to serum albumin (approximately 98.5 %) and induces an increase in the serum concentrations of both SHBG and CBG. EE induced effects on SHBG and CBG were not affected by variation of the DRSP dosage in the range of 2 to 3 mg.

Biphasic kinetics is reported for folates with a fast- and a slow-turnover pool. The fast-turnover pool, probably reflecting newly absorbed folate, is consistent with the terminal half-life of approximately 4–5 hours after single oral administration of 0.451 mg levomefolate calcium. The slow-turnover pool reflecting turnover of folate polyglutamate has a mean residence time of greater than or equal to 100 days.

Metabolism

The two main metabolites of DRSP found in human plasma were identified to be the acid form of DRSP generated by opening of the lactone ring and the 4,5-dihydrodrospirenone-3-sulfate, formed by reduction and subsequent sulfatation. These metabolites were shown not to be pharmacologically active. Drospirenone is also subject to oxidative metabolism catalyzed by CYP3A4.

EE has been reported to be subject to significant gut and hepatic first-pass metabolism. Metabolism of EE and its oxidative metabolites occur primarily by conjugation with glucuronide or sulfate. CYP3A4 in the liver is responsible for the 2-hydroxylation which is the major oxidative reaction. The 2-hydroxy metabolite is further transformed by methylation and glucuronidation prior to urinary and fecal excretion.

L-5-methyl-THF is the predominant folate transport form in blood under physiological conditions and during folic acid and levomefolate calcium administration.

Excretion

DRSP serum concentrations are characterized by a terminal disposition phase half-life of approximately 30 hours after both single and multiple dose regimens. Excretion of DRSP was nearly complete after ten days and amounts excreted were slightly higher in feces compared to urine. DRSP was extensively metabolized and only trace amounts of unchanged DRSP were excreted in urine and feces. At least 20 different metabolites were observed in urine and feces. About 38–47% of the metabolites in urine were glucuronide and sulfate conjugates. In feces, about 17–20% of the metabolites were excreted as glucuronides and sulfates.

For EE the terminal disposition phase half-life has been reported to be approximately 24 hours. EE is not excreted unchanged. EE is excreted in the urine and feces as glucuronide and sulfate conjugates and undergoes enterohepatic circulation.

L-5-methyl-THF is eliminated from the body by urinary excretion of intact folates and catabolic products as well as fecal excretion through a biphasic kinetics process.

Use in Specific Populations

Pediatric Use: Safety and efficacy of Safyral has been established in women of reproductive age. Efficacy is expected to be the same for postpubertal adolescents under the age of 18 and for users 18 years and older. Use of this product before menarche is not indicated.

Geriatric Use: Safyral has not been studied in postmenopausal women and is not indicated in this population. Race: No clinically significant difference was observed between the pharmacokinetics of DRSP or EE in Japanese versus Caucasian women (age 25–35) when 3 mg DRSP/0.02 mg EE was administered daily for 21 days. Other ethnic groups have not been specifically studied.

Renal Impairment: Safyral is contraindicated in patients with renal impairment.

The effect of renal impairment on the pharmacokinetics of DRSP (3 mg daily for 14 days) and the effect of DRSP on serum potassium concentrations were investigated in three separate groups of female subjects (n=28, age 30-65). All subjects were on a low potassium diet. During the study, 7 subjects continued the use of potassium-sparing drugs for the treatment of their underlying illness. On the 14th day (steady-state) of DRSP treatment, the serum DRSP concentrations in the group with CLcr of 50–79 mL/min were comparable to those in the control group with CLcr ≥ 80 mL/min. The serum DRSP concentrations were on average 37% higher in the group with CLcr of 30–49 mL/min compared to those in the control group. DRSP treatment did not show any clinically significant effect on serum potassium concentration. Although hyperkalemia was not observed in the study, in five of the seven subjects who continued use of potassium-sparing drugs during the study, mean serum potassium concentrations increased by up to 0.33 mEq/L. [See Contraindications (4) and Warnings and Precautions (5.2).]

Hepatic Impairment: Safyral is contraindicated in patients with hepatic disease.

The mean exposure to DRSP in women with moderate liver impairment is approximately three times higher than the exposure in women with normal liver function. Safyral has not been studied in women with severe hepatic impairment. [See Contraindications (4) and Warnings and Precautions (5.4).]

Drug Interactions

Consult the labeling of all concurrently used drugs to obtain further information about interactions with oral contraceptives or the potential for enzyme alterations.

Effects of Other Drugs on Combined Oral Contraceptives

Substances diminishing the efficacy of COCs: Drugs or herbal products that induce certain enzymes, including CYP3A4, may decrease the effectiveness of COCs or increase breakthrough bleeding.

Substances increasing the plasma concentrations of COCs: Co-administration of atorvastatin with certain COCs containing EE increase AUC values for EE by approximately 20%. Ascorbic acid and acetaminophen may increase plasma EE concentrations, possibly by inhibition of conjugation. In a clinical drug-drug interaction study conducted in 20 premenopausal women, co-administration of a DRSP (3 mg)/EE (0.02 mg) COC with the strong CYP3A4 inhibitor ketoconazole (200 mg twice daily) for 10 days increased the AUC(0-24h) of DRSP and EE by 2.68-fold (90% CI: 2.44, 2.95) and 1.40-fold (90% CI: 1.31, 1.49), respectively. The increases in Cmax were 1.97-fold (90% CI: 1.79, 2.17) and 1.39-fold (90% CI: 1.28, 1.52) for DRSP and EE, respectively. Although no clinically relevant effects on safety or laboratory parameters including serum potassium were observed, this study only assessed subjects for 10 days. The clinical impact for a patient taking a DRSP-containing COC concomitantly with chronic use of a CYP3A4/5 inhibitor is unknown [see Warnings and Precautions (5.2)].

HIV/HCV protease inhibitors and non-nucleoside reverse transcriptase inhibitors: Significant changes (increase or decrease) in the plasma concentrations of estrogen and progestin have been noted in some cases of co-administration with HIV/HCV protease inhibitors or with non-nucleoside reverse transcriptase inhibitors.

Antibiotics: There have been reports of pregnancy while taking hormonal contraceptives and antibiotics, but clinical pharmacokinetic studies have not shown consistent effects of antibiotics on plasma concentrations of synthetic steroids.

Effects of Combined Oral Contraceptives on Other Drugs

COCs containing EE may inhibit the metabolism of other compounds. COCs have been shown to significantly decrease plasma concentrations of lamotrigine, likely due to induction of lamotrigine glucuronidation. This may reduce seizure control; therefore, dosage adjustments of lamotrigine may be necessary. Consult the labeling of the concurrently-used drug to obtain further information about interactions with COCs or the potential for enzyme alterations.

In vitro, EE is a reversible inhibitor of CYP2C19, CYP1A1 and CYP1A2 as well as a mechanism-based inhibitor of CYP3A4/5, CYP2C8, and CYP2J2. Metabolism of DRSP and potential effects of DRSP on hepatic CYP enzymes have been investigated in in vitro and in vivo studies. In in vitro studies DRSP did not affect turnover of model substrates of CYP1A2 and CYP2D6, but had an inhibitory influence on the turnover of model substrates of CYP1A1, CYP2C9, CYP2C19, and CYP3A4, with CYP2C19 being the most sensitive enzyme. The potential effect of DRSP on CYP2C19 activity was investigated in a clinical pharmacokinetic study using omeprazole as a marker substrate. In the study with 24 postmenopausal women [including 12 women with homozygous (wild type) CYP2C19 genotype and 12 women with heterozygous CYP2C19 genotype] the daily oral administration of 3 mg DRSP for 14 days did not affect the oral clearance of omeprazole (40 mg, single oral dose) and the CYP2C19 product 5-hydroxy omeprazole. Furthermore, no significant effect of DRSP on the systemic clearance of the CYP3A4 product omeprazole sulfone was found. These results demonstrate that DRSP did not inhibit CYP2C19 and CYP3A4 in vivo.

Two additional clinical drug-drug interaction studies using simvastatin and midazolam as marker substrates for CYP3A4 were each performed in 24 healthy postmenopausal women. The results of these studies demonstrated that pharmacokinetics of the CYP3A4 substrates were not influenced by steady state DRSP concentrations achieved after administration of 3 mg DRSP/day.

Women on thyroid hormone replacement therapy may need increased doses of thyroid hormone because serum concentration of thyroid-binding globulin increases with use of COCs.

Interactions With Drugs That Have the Potential to Increase Serum Potassium

Concentration: There is a potential for an increase in serum potassium concentration in women taking Safyral with other drugs that may increase serum potassium concentration [see Warnings and Precautions (5.2)].

A drug-drug interaction study of DRSP 3 mg/estradiol (E2) 1 mg versus placebo was performed in 24 mildly hypertensive postmenopausal women taking enalapril maleate 10 mg twice daily. Potassium concentrations were obtained every other day for a total of 2 weeks in all subjects. Mean serum potassium concentrations in the DRSP/E2 treatment group relative to baseline were 0.22 mEq/L higher than those in the placebo group. Serum potassium concentrations also were measured at multiple time points over 24 hours at baseline and on Day 14. On Day 14, the ratios for serum potassium Cmax and AUC in the DRSP/E2 group to those in the placebo group were 0.955 (90% CI: 0.914, 0.999) and 1.010 (90% CI: 0.944, 1.08), respectively. No patient in either treatment group developed hyperkalemia (serum potassium concentrations >5.5 mEq/L).

Effects of Folates on Other Drugs

There is a potential that folates such as folic acid and levomefolate calcium may modify the pharmacokinetics or pharmacodynamics of certain antifolate drugs (e.g., antiepileptics, methotrexate).

Effects of other Drugs on Folate

Several drugs (e.g., methotrexate, sulfasalazine, cholestyramine, antiepileptics) have been reported to reduce folate concentrations.

13 NONCLINICAL TOXICOLOGY

13.1 Carcinogenesis, Mutagenesis, Impairment of Fertility

In a 24 month oral carcinogenicity study in mice dosed with 10 mg/kg/day DRSP alone or 1 + 0.01, 3+ 0.03 and 10 + 0.1 mg/kg/day of DRSP and EE, 0.1 to 2 times the exposure (AUC of DRSP) of women taking a contraceptive dose, there was an increase in carcinomas of the harderian gland in the group that received the high dose of DRSP alone. In a similar study in rats given 10 mg/kg/day DRSP alone or 0.3 + 0.003, 3 + 0.03 and 10 + 0.1 mg/kg/day DRSP and EE, 0.8 to 10 times the exposure of women taking a contraceptive dose, there was an increased incidence of benign and total (benign and malignant) adrenal gland pheochromocytomas in the group receiving the high dose of DRSP. Mutagenesis studies for DRSP were conducted in vivo and in vitro and no evidence of mutagenic activity was observed [see Warnings and Precautions (5.3, 5.4)].

Long-term animal studies have not been conducted to evaluate the carcinogenic potential of levomefolate. Mutagenesis studies for levomefolate were conducted in vitro and in vivo and no evidence of mutagenic activity was observed.

14 CLINICAL STUDIES

14.1 Oral Contraceptive Clinical Trial

In the clinical efficacy studies of Yasmin (3 mg DRSP/0.03 mg EE) of up to 2 years duration, 2,629 subjects completed 33,160 cycles of use without any other contraception. The mean age of the subjects was 25.5 ± 4.7 years. The age range was 16 to 37 years. The racial demographic was: 83% Caucasian, 1% Hispanic, 1% Black, <1% Asian, <1% other, <1% missing data, 14% not inquired and <1% unspecified. Pregnancy rates in the clinical trials were less than one per 100 woman-years of use.

14.2 Folate Supplementation Clinical Trials

The development program for Safyral (Yasmin + levomefolate calcium) consisted of two clinical trials.

One study was a multicenter, randomized, double-blind, active-controlled, parallel group US study. Plasma folate and red blood cell folate levels were investigated during a 24-week treatment with 3 mg DRSP/0.02 mg EE (YAZ) + 0.451 mg levomefolate calcium as compared to YAZ alone in a U.S. population that consumed folate fortified food. A total of 379 healthy women between 18 and 40 years of age with no restrictions on folate supplementation received YAZ + levomefolate calcium (N= 285) or YAZ (N=94). The plasma and RBC folate concentrations at Week 24 were the co-primary endpoints. Figures 4 and 5 display the results for plasma and RBC folate concentrations, respectively, among evaluable subjects in each arm of the study.

Figure 4: US Study: Mean trough concentration-time curves (and SD) of plasma folates after daily oral administration of YAZ + levomefolate calcium and YAZ

Arithmetic mean values based on 4‑weekly measurements are displayed with arithmetic standard deviations which are shown in only one direction to improve readability. Data are based on the per protocol analysis populations. The SD bars shown represent one SD.

Figure 5: US Study: Mean concentration-time curves (and SD) of RBC folates after daily oral administration of YAZ + levomefolate calcium and YAZ

Arithmetic mean values based on 4‑weekly measurements are displayed with arithmetic standard deviations which are shown in only one direction to improve readability. Data are based on the per protocol analysis populations. The SD bars shown represent one SD.

In the second study, the pharmacodynamic effect on plasma folate, RBC folate, and the profile of circulating folate metabolites was assessed during 24 weeks of treatment with 0.451 mg levomefolate calcium or with 0.4 mg folic acid (equimolar dose to 0.451 mg levomefolate calcium), both in combination with 3 mg DRSP/0.03 mg EE (Yasmin) followed by 20 weeks of open-label treatment with Yasmin only (elimination phase). One-hundred and seventy-two healthy women between 18 to 40 years of age from a German population that consumed food without folate fortification and without concomitant intake of folate supplements were randomized to one of the two treatments. Figures 6 and 7 display the results for plasma and RBC folate concentrations, respectively, among evaluable subjects in the levomefolate arm of the study.

Figure 6: German Study: Mean trough concentration-time curve (and SD) of plasma folates after daily oral administration of Yasmin + levomefolate calcium

Arithmetic mean values based on biweekly measurements are displayed with arithmetic standard deviations. In the treatment phase, women received Yasmin + levomefolate calcium; in the elimination phase, all women received Yasmin only. Data are based on the per protocol analysis population. The SD bars shown represent one SD.

Figure 7: German Study: Mean concentration-time curves (and SD) of RBC folates after daily oral administration of Yasmin + levomefolate calcium

Arithmetic mean values based on biweekly measurements are displayed with arithmetic standard deviations. In the treatment phase, women received Yasmin + levomefolate calcium; in the elimination phase, all women received Yasmin only. Data are based on the per protocol analysis population. The SD bars shown represent one SD.

The potential to reduce the incidence of neural tube defects (NTDs) with folate supplementation is well established based on a body of evidence derived from randomized, controlled trials, nonrandomized intervention trials, and observational studies using folic acid. Therefore, the Centers for Disease Control and Prevention (CDC) and the U.S. Preventive Services Task Force recommend that women of childbearing age consume supplemental folic acid in a dose of at least 0.4 mg (400 mcg) daily ^1,6.

15 REFERENCES

1. US Preventive Services Task Force. Folic Acid for the Prevention of Neural Tube Defects: US Preventive Services Task Force Recommendation Statement. Ann Intern Med 2009;150:626-631.
2. Seeger, J.D., Loughlin, J., Eng, P.M., Clifford, C.R., Cutone, J., and Walker, A.M. (2007). Risk of thromboembolism in women taking ethinylestradiol/drospirenone and other oral contraceptives. Obstet Gynecol 110, 587-593.
3. Dinger, J.C., Heinemann, L.A., and Kuhl-Habich, D. (2007). The safety of a drospirenone-containing oral contraceptive: final results from the European Active Surveillance Study on oral contraceptives based on 142,475 women-years of observation. Contraception 75, 344-354.
4. Combined hormonal contraceptives (CHCs) and the risk of cardiovascular endpoints. Sidney, S. (primary author) http://www.fda.gov/downloads/Drugs/DrugSafety/UCM277384.pdf, accessed Oct 27, 2011.
5. Lidegaard, O., Lokkegaard, E., Svendsen, A.L., and Agger, C. (2009). Hormonal contraception and risk of venous thromboembolism: national follow-up study. BMJ 339, b2890.
6. Lidegaard, O., Nielsen, L.H., Skovlund, C.W., Skjeldestad, F.E., and Lokkegaard, E. (2011). Risk of venous thromboembolism from use of oral contraceptives containing different progestogens and oestrogen doses: Danish cohort study, 2001-9. BMJ 343, d6423.
7. van Hylckama Vlieg, A., Helmerhorst, F.M., Vandenbroucke, J.P., Doggen, C.J., and Rosendaal, F.R. (2009). The venous thrombotic risk of oral contraceptives, effects of oestrogen dose and progestogen type: results of the MEGA case-control study. BMJ 339, b2921.
8. Dinger, J., Assmann, A., Mohner, S., and Minh, T.D. (2010). Risk of venous thromboembolism and the use of dienogest- and drospirenone-containing oral contraceptives: results from a German case-control study. J Fam Plann Reprod Health Care 36, 123-129.
9. Jick, S.S., and Hernandez, R.K. (2011). Risk of non-fatal venous thromboembolism in women using oral contraceptives containing drospirenone compared with women using oral contraceptives containing levonorgestrel: case-control study using United States claims data. BMJ 342, d2151.
10. Parkin, L., Sharples, K., Hernandez, R.K., and Jick, S.S. (2011). Risk of venous thromboembolism in users of oral contraceptives containing drospirenone or levonorgestrel: nested case-control study based on UK General Practice Research Database. BMJ 342, d2139.
11. Centers for Disease Control. Recommendations for the use of folic acid to reduce the number of cases of spina bifida and other neural tube defects. MMWR 1992;41(No. RR-14).

16 HOW SUPPLIED/STORAGE AND HANDLING

16.1 How Supplied

Safyral (drospirenone/ethinyl estradiol/levomefolate calcium tablets and levomefolate calcium tablets) is available in packages of three blister packs (NDC 50419-403-03).

The film-coated tablets are rounded with biconvex faces, one side is embossed with a regular hexagon shape with Y+ or M+.

Each blister pack contains 28 film-coated tablets in the following order:

- 21 round, biconvex, orange, film-coated tablets with embossed “Y+” in a regular hexagon on one side each containing 3 mg drospirenone, 0.03 mg ethinyl estradiol, and 0.451 mg levomefolate calcium
- 7 round, biconvex, light orange, film-coated tablets with embossed “M+” in a regular hexagon on one side each containing 0.451 mg levomefolate calcium

16.2 Storage

Store at 25ºC (77°F); excursions permitted to 15–30ºC (59–86ºF) [see USP Controlled Room Temperature].

17 PATIENT COUNSELING INFORMATION

Advise the patient to read the FDA-approved patient labeling (Patient Information).

- Counsel patients that cigarette smoking increases the risk of serious cardiovascular events from COC use, and that women who are over 35 years old and smoke should not use COCs.
- Counsel patients that the increased risk of VTE compared to non-users of COCs is greatest after initially starting a COC or restarting (following a 4-week or greater pill-free interval) the same or a different COC.
- Counsel patients about the information regarding the risk of VTE with DRSP-containing COCs compared to COCs that contain levonorgestrel or some other progestins.
- Counsel patients that Safyral does not protect against HIV-infection (AIDS) and other sexually transmitted diseases.
- Counsel patients on Warnings and Precautions associated with COCs.
- Counsel patients that Safyral contains DRSP. Drospirenone may increase potassium. Patients should be advised to inform their healthcare provider if they have kidney, liver or adrenal disease because the use of Safyral in the presence of these conditions could cause serious heart and health problems. They should also inform their healthcare provider if they are currently on daily, long-term treatment (NSAIDs, potassium-sparing diuretics, potassium supplementation, ACE inhibitors, angiotensin-II receptor antagonists, heparin or aldosterone antagonists) for a chronic condition or taking strong CYP3A4 inhibitors.
- Inform patients that Safyral is not indicated during pregnancy. If pregnancy occurs during treatment with Safyral, instruct the patient to stop further intake. However, women should be advised on the continued need of sufficient folate intake.
- Counsel patients to take one tablet daily by mouth at the same time every day. Instruct patients what to do in the event pills are missed.
- Counsel patients to use a back-up or alternative method of contraception when enzyme inducers are used with COCs.
- Counsel patients who are breastfeeding or who desire to breastfeed that COCs may reduce breast milk production. This is less likely to occur if breastfeeding is well established.
- Counsel any patient who starts COCs postpartum, and who has not yet had a period, to use an additional method of contraception until she has taken an orange tablet for 7 consecutive days.
- Counsel patients that amenorrhea may occur. Rule out pregnancy in the event of amenorrhea in two or more consecutive cycles.
- Counsel patients to report whether they are taking folate supplements. Safyral contains the equivalent of 0.4 mg (400 mcg) of folic acid.
- Counsel patients to maintain folate supplementation if they discontinue Safyral due to pregnancy.

FDA Approved Patient Labeling

Guide for Using Safyral

WARNING TO WOMEN WHO SMOKE

Do not use Safyral if you smoke cigarettes and are over 35 years old. Smoking increases your risk of serious cardiovascular side effects (heart and blood vessel problems) from birth control pills, including death from heart attack, blood clots or stroke. This risk increases with age and the number of cigarettes you smoke.

Birth control pills help to lower the chances of becoming pregnant when taken as directed. They do not protect against HIV infection (AIDS) and other sexually transmitted diseases.

What Is Safyral?

Safyral is a birth control pill. It contains two female hormones, a synthetic estrogen called ethinyl estradiol and a progestin called drospirenone. Safyral also contains levomefolate calcium, which is a B vitamin.

The progestin drospirenone may increase potassium. Therefore, you should not take Safyral if you have kidney, liver or adrenal disease because this could cause serious heart and health problems. Other drugs may also increase potassium. If you are currently on daily, long-term treatment for a chronic condition with any of the medications below, you should consult your healthcare provider about whether Safyral is right for you, and during the first month that you take Safyral, you should have a blood test to check your potassium level.

- NSAIDs (ibuprofen [Motrin, Advil], naproxen [Aleve and others] when taken long-term and daily for treatment of arthritis or other problems)
- Potassium-sparing diuretics (spironolactone and others)
- Potassium supplementation
- ACE inhibitors (Capoten, Vasotec, Zestril and others)
- Angiotensin-II receptor antagonists (Cozaar, Diovan, Avapro and others)
- Heparin
- Aldosterone antagonists

Safyral may also be taken by women who elect to use an oral contraceptive, to provide folate supplementation. It is recommended that women of reproductive age supplement their diet with 0.4 mg (400 mcg) of folic acid daily to lower their risk of having a pregnancy with a rare type of birth defect (known as a neural tube defect). The amount of folate contained in Safyral supplements folate in the diet to lower this risk should you become pregnant while taking the drug or shortly after stopping it.

How Well Does Safyral Work?

Your chance of getting pregnant depends on how well you follow the directions for taking your birth control pills. The better you follow the directions, the less chance you have of getting pregnant.

Based on the results of two clinical studies, about1 woman out of 100 women, may get pregnant during the first year they use Safyral.

The following chart shows the chance of getting pregnant for women who use different methods of birth control. Each box on the chart contains a list of birth control methods that are similar in effectiveness. The most effective methods are at the top of the chart. The box on the bottom of the chart shows the chance of getting pregnant for women who do not use birth control and are trying to get pregnant.

How Do I Take Safyral?

1. Be sure to read these directions before you start taking your pills or anytime you are not sure what to do.

2. The right way to take the pill is to take one pill every day at the same time in the order directed on the package. Preferably, take the pill after the evening meal or at bedtime, with some liquid, as needed. Safyral can be taken without regard to meals.

If you miss pills you could get pregnant. This includes starting the pack late. The more pills you miss, the more likely you are to get pregnant. See "WHAT TO DO IF YOU MISS PILLS” below.

3. Many women have spotting or light bleeding at unexpected times, or may feel sick to their stomach during the first 1-3 packs of pills.

If you do have spotting or light bleeding or feel sick to your stomach, do not stop taking the pill. The problem will usually go away. If it does not go away, check with your healthcare provider.

4. Missing pills can also cause spotting or light bleeding, even when you make up these missed pills.

On the days you take two pills, to make up for missed pills, you could also feel a little sick to your stomach.

5. If you have vomiting (within 3 to 4 hours after you take your pill), you should follow the instructions for "WHAT TO DO IF YOU MISS PILLS." If you have diarrhea or if you take certain medicines, including some antibiotics and some herbal products such as St. John's Wort, your pills may not work as well.

Use a back-up method (such as condoms and spermicides) until you check with your healthcare provider.

6. If you have trouble remembering to take the pill, talk to your healthcare provider about how to make pill-taking easier or about using another method of birth control.

7. If you have any questions or are unsure about the information in this leaflet, call your healthcare provider.

Before You Start Taking Your Pills

1. Decide What Time of Day You Want to Take Your Pill

It is important to take Safyral in the order directed on the package at the same time every day, preferably after the evening meal or at bedtime, with some liquid, as needed. Safyral can be taken without regard to meals.

2. Look at Your Pill Pack – It has 28 Pills

The Safyral pill pack has 21 orange pills (with hormones and folate) to be taken for three weeks, followed by 7 light orange pills (without hormones, containing folate) to be taken for one week. It is important to take the light orange pills because they contain folate.

3. Also look for:

a) Where on the pack to start taking pills,

b) In what order to take the pills (follow the arrows)

4. Be sure you have ready at all times (a) another kind of birth control (such as condoms and spermicides) to use as a back-up in case you miss pills, and (b) an extra, full pill pack.

When To Start the First Pack of Pills

You have a choice for which day to start taking your first pack of pills. Decide with your healthcare provider which is the best day for you. Pick a time of day which will be easy to remember.

Day 1 Start:

1. Take the first orange pill of the pack during the first 24 hours of your period.

2. You will not need to use a back-up method of birth control, because you are starting the Pill at the beginning of your period. However, if you start Safyral later than the first day of your period, you should use another method of birth control (such as a condom and spermicide) as a back-up method until you have taken 7 orange pills.

Sunday Start:

1. Take the first orange pill of the pack on the Sunday after your period starts, even if you are still bleeding. If your period begins on Sunday, start the pack that same day.

2. Use another method of birth control (such as a condom and spermicide) as a back-up method if you have sex anytime from the Sunday you start your first pack until the next Sunday (7 days). This also applies if you start Safyral after having been pregnant and you have not had a period since your pregnancy.

When You Switch From a Different Birth Control Pill

When switching from another birth control pill, Safyral should be started on the same day that a new pack of the previous birth control pill would have been started.

When You Switch From Another Type of Birth Control Method

When switching from a transdermal patch or vaginal ring, Safyral should be started when the next application would have been due. When switching from an injection, Safyral should be started when the next dose would have been due. When switching from an intrauterine contraceptive or an implant, Safyral should be started on the day of removal.

What to Do During the Month

1. Take one pill at the same time every day until the pack is empty.

Do not skip pills even if you are spotting or bleeding between monthly periods or feel sick to your stomach (nausea).

Do not skip pills even if you do not have sex very often.

2. When you finish a pack of pills, start the next pack on the day after your last light orange pill. It is important to take the light orange pills because they contain folate. Do not wait any days between packs.

What to Do if You Miss Pills

If you miss 1 orange pill of your pack:

1. Take it as soon as you remember. Take the next pill at your regular time. This means you may take two pills in one day.

2. You do not need to use a back-up birth control method if you have sex.

If you miss 2 orange pills in a row in Week 1 or Week 2 of your pack:

1. Take two pills on the day you remember and two pills the next day.

2. Then take one pill a day until you finish the pack.

3. You could become pregnant if you have sex in the 7 days after you restart your pills. You must use another birth control method (such as a condom and spermicide) as a back-up for those 7 days.

If you miss 2 orange pills in a row in Week 3 of your pack:

1. If you are a Day 1 Starter:

Throw out the rest of the pill pack and start a new pack that same day.

2. If you are a Sunday Starter:

Keep taking one pill every day until Sunday. On Sunday, throw out the rest of the pack and start a new pack of pills that same day.

3. You could become pregnant if you have sex in the 7 days after you restart your pills. You must use another birth control method (such as a condom and spermicide) as a back-up for those 7 days.

4. You may not have your period this month but this is expected. However, if you miss your period two months in a row, call your healthcare provider because you might be pregnant.

If you miss 3 or more orange pills in a row during any week:

1. If you are a Day 1 Starter:

Throw out the rest of the pill pack and start a new pack that same day.

2. If you are a Sunday Starter:

Keep taking 1 pill every day until Sunday. On Sunday, throw out the rest of the pack and start a new pack of pills that same day.

3. You could become pregnant if you have sex in the 7 days after you restart your pills. You must use another birth control method (such as condoms and spermicides) as a back-up for those 7 days.

4. You may not have your period this month but this is expected. However, if you miss your period two months in a row, call your healthcare provider because you might be pregnant.

If you miss any of the 7 light orange pills in Week 4:

Throw away the pills you missed.

Keep taking one pill each day until the pack is empty.

You do not need a back-up method.

Finally, if you are still not sure what to do about the pills you have missed:

Use a back-up method (such as condoms and spermicides) anytime you have sex.

Contact your healthcare provider and continue taking one active orange pill each day until otherwise directed.

WHO SHOULD NOT TAKE Safyral?

Your healthcare provider will not give you Safyral if you:

• Ever had blood clots in your legs (deep vein thrombosis), lungs (pulmonary embolism), or eyes (retinal thrombosis)

• Ever had a stroke

• Ever had a heart attack

• Have certain heart valve problems or heart rhythm abnormalities that can cause blood clots to form in the heart

• Have an inherited problem with your blood that makes it clot more than normal

• Have high blood pressure that medicine can’t control

• Have diabetes with kidney, eye, nerve, or blood vessel damage

• Ever had certain kinds of severe migraine headaches with aura, numbness, weakness or changes in vision

• Ever had breast cancer which may be sensitive to female hormones

• Have liver disease, including liver tumors

• Take any Hepatitis C drug combination containing ombitasvir/paritaprevir/ritonavir, with or without dasabuvir. This may increase levels of the liver enzyme “alanine aminotransferase” (ALT) in the blood.

• Have kidney disease

• Have adrenal disease

Also, do not take birth control pills if you:

• Smoke and are over 35 years old

• Are or suspect you are pregnant

Birth control pills may not be a good choice for you if you have ever had jaundice (yellowing of the skin or eyes) caused by pregnancy (also called cholestasis of pregnancy).

Tell your healthcare provider if you have ever had any of the above conditions (your healthcare provider can recommend another method of birth control).

Tell your healthcare provider if you are already taking daily folate supplements.

What Else Should I Know about Taking Safyral?

Birth control pills do not protect you against any sexually transmitted disease, including HIV, the virus that causes AIDS.

Do not skip any pills, even if you do not have sex often.

If you miss a period, you could be pregnant. However, some women miss periods or have light periods on birth control pills, even when they are not pregnant. Contact your healthcare provider for advice if you:

- Think you are pregnant
- Miss one period and have not taken your birth control pills on time every day
- Miss two periods in a row

Birth control pills should not be taken during pregnancy. However, birth control pills taken by accident during pregnancy are not known to cause birth defects.

Due to an increased risk of blood clots, you should stop Safyral at least four weeks before you have major surgery and not restart it until at least two weeks after the surgery.

If you are breastfeeding, consider another birth control method until you are ready to stop breastfeeding. Birth control pills that contain estrogen, like Safyral, may decrease the amount of milk you make. A small amount of the pill's hormones pass into breast milk.

Folates may make certain drugs, including some used for epilepsy, less effective, so talk to your healthcare provider about any medicines you take.

If you have vomiting or diarrhea, your birth control pills may not work as well. Take another pill if you vomit within 3-4 hours after taking your pill, or use another birth control method, like condoms and a spermicide, until you check with your healthcare provider.

If you are scheduled for any laboratory tests, tell your doctor you are taking birth-control pills. Certain blood tests may be affected by birth-control pills.

Tell your healthcare provider about all the medicines you take, including prescription and over-the-counter medicines, vitamins and herbal supplements.

Safyral may affect the way other medicines work, and other medicines may affect how well Safyral works. Know the medicines you take.

Keep a list of them to show your healthcare provider and pharmacist when you get a new medicine.

What are the Most Serious Risks of Taking Birth Control Pills?

Like pregnancy, birth control pills increase the risk of serious blood clots (see following graph), especially in women who have other risk factors, such as smoking, obesity, or age greater than 35. This increased risk is highest when you first start taking birth control pills and when you restart the same or different birth control pills after not using them for a month or more. Women who use birth control pills with drospirenone (like Safyral) may have a higher risk of getting a blood clot. Some studies reported that the risk of blood clots was higher for women who use birth control pills that contain drospirenone than for women who use birth control pills that do not contain drospirenone.

Talk with your healthcare provider about your risk of getting a blood clot before deciding which birth control pill is right for you.

It is possible to die or be permanently disabled from a problem caused by a blood clot, such as a heart attack or a stroke. Some examples of serious clots are blood clots in the:

- Legs (deep vein thrombosis or DVT)
- Lungs (pulmonary embolus or PE)
- Eyes (loss of eyesight)
- Heart (heart attack)
- Brain (stroke)

To put the risk of developing a blood clot into perspective: If 10,000 women who are not pregnant and do not use birth control pills are followed for one year, between 1 and 5 of these women will develop a blood clot. The figure below shows the likelihood of developing a serious blood clot for women who are not pregnant and do not use birth control pills, for women who use birth control pills, for pregnant women, and for women in the first 12 weeks after delivering a baby.

Likelihood of Developing a Serious Blood Clot

A few women who take birth control pills may get:

- High blood pressure
- Gallbladder problems
- Rare cancerous or noncancerous liver tumors

All of these events are uncommon in healthy women.

Call your healthcare provider right away if you have:

- Persistent leg pain
- Sudden shortness of breath
- Sudden blindness, partial or complete
- Severe pain in your chest
- Sudden, severe headache unlike your usual headaches
- Weakness or numbness in an arm or leg, or trouble speaking
- Yellowing of the skin or eyeballs

What are the Common Side Effects of Birth Control Pills?

The most common side effects of birth control pills are:

- Spotting or bleeding between menstrual periods
- Nausea
- Breast tenderness
- Headache

These side effects are usually mild and usually disappear with time.

Less common side effects are:

- Acne
- Less sexual desire
- Bloating or fluid retention
- Blotchy darkening of the skin, especially on the face
- High blood sugar, especially in women who already have diabetes
- High fat (cholesterol; triglyceride) levels in the blood
- Depression, especially if you have had depression in the past. Call your healthcare provider immediately if you have any thoughts of harming yourself.
- Problems tolerating contact lenses
- Weight changes

This is not a complete list of possible side effects. Talk to your healthcare provider if you develop any side effects that concern you. You may report side effects to the FDA at 1-800-FDA-1088.

No serious problems have been reported from a birth control pill overdose, even when accidentally taken by children.

Do Birth Control Pills Cause Cancer?

It is not known if hormonal birth control pills cause breast cancer. Some studies, but not all, suggest that there could be a slight increase in the risk of breast cancer among current users with longer duration of use.

If you have breast cancer now, or have had it in the past, do not use hormonal birth control because some breast cancers are sensitive to hormones.

Women who use birth control pills may have a slightly higher chance of getting cervical cancer. However, this may be due to other reasons such as having more sexual partners.

What Should I Know about My Period when Taking Safyral?

Irregular vaginal bleeding or spotting may occur while you are taking Safyral. Irregular bleeding may vary from slight staining between menstrual periods to breakthrough bleeding, which is a flow much like a regular period. Irregular bleeding occurs most often during the first few months of oral contraceptive use, but may also occur after you have been taking the pill for some time. Such bleeding may be temporary and usually does not indicate any serious problems. It is important to continue taking your pills on schedule. If the bleeding occurs in more than one cycle, is unusually heavy, or lasts for more than a few days, call your healthcare provider.

Some women may not have a menstrual period but this should not be cause for alarm as long as you have taken the pills regularly on time.

What if I Miss My Scheduled Period when Taking Safyral?

It is not uncommon to miss your period. However, if you miss two periods in a row or miss one period when you have not taken your birth control pills regularly on time, call your healthcare provider. Also notify your healthcare provider if you have symptoms of pregnancy such as morning sickness or unusual breast tenderness. It is important that your healthcare provider checks you to find out if you are pregnant. Stop taking Safyral if you are pregnant.

What If I Want to Become Pregnant?

You may stop taking the pill whenever you wish. Consider a visit with your healthcare provider for a pre-pregnancy checkup before you stop taking the pill. See your healthcare provider about appropriate folate supplementation if you stop taking Safyral, are pregnant, or plan on becoming pregnant.

General Advice about Safyral

Your healthcare provider prescribed Safyral for you. Please do not share Safyral with anyone else. Keep Safyral out of the reach of children.

If you have concerns or questions, ask your healthcare provider. You may also ask your healthcare provider for a more detailed label written for medical professionals.

Manufactured for:
Bayer HealthCare Pharmaceuticals Inc.
Whippany, NJ 07981

Manufactured in Germany

©2010 Bayer HealthCare Pharmaceuticals Inc. All Rights Reserved

Bayer HealthCare Pharmaceuticals Inc.

PACKAGE/LABEL PRINCIPAL DISPLAY PANEL

SAFYRAL Trade Carton

NDA 50419-403-01

1 Unit

Rx only

This product (like all oral contraceptives) in intended to prevent pregnancy. It does not protect against HIV infection (AIDS) and other sexually transmitted diseases.

SAFYRAL™

(drospirenone/ethinyl estradiol/levomefolate calcium tablets and levomefolate calcium tablets)

3mg/0.03 mg/0.451 mg and 0.451 mg

28 tablets

Oral